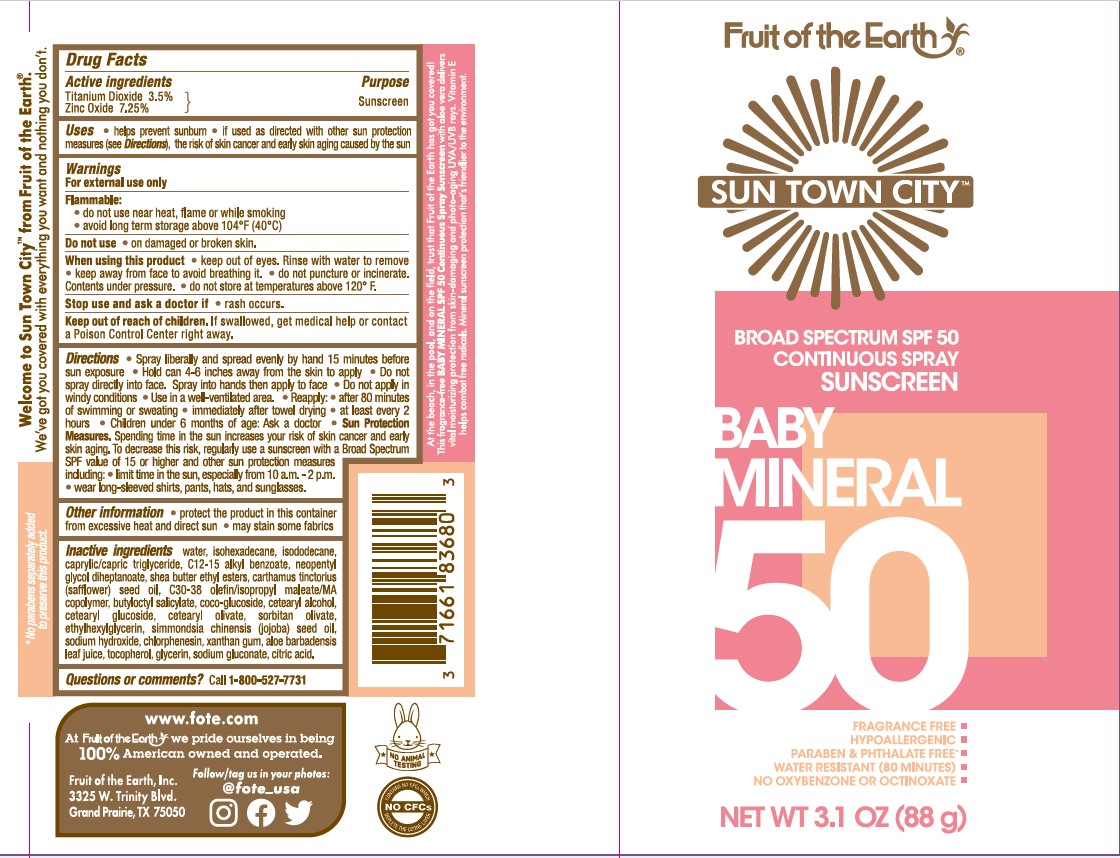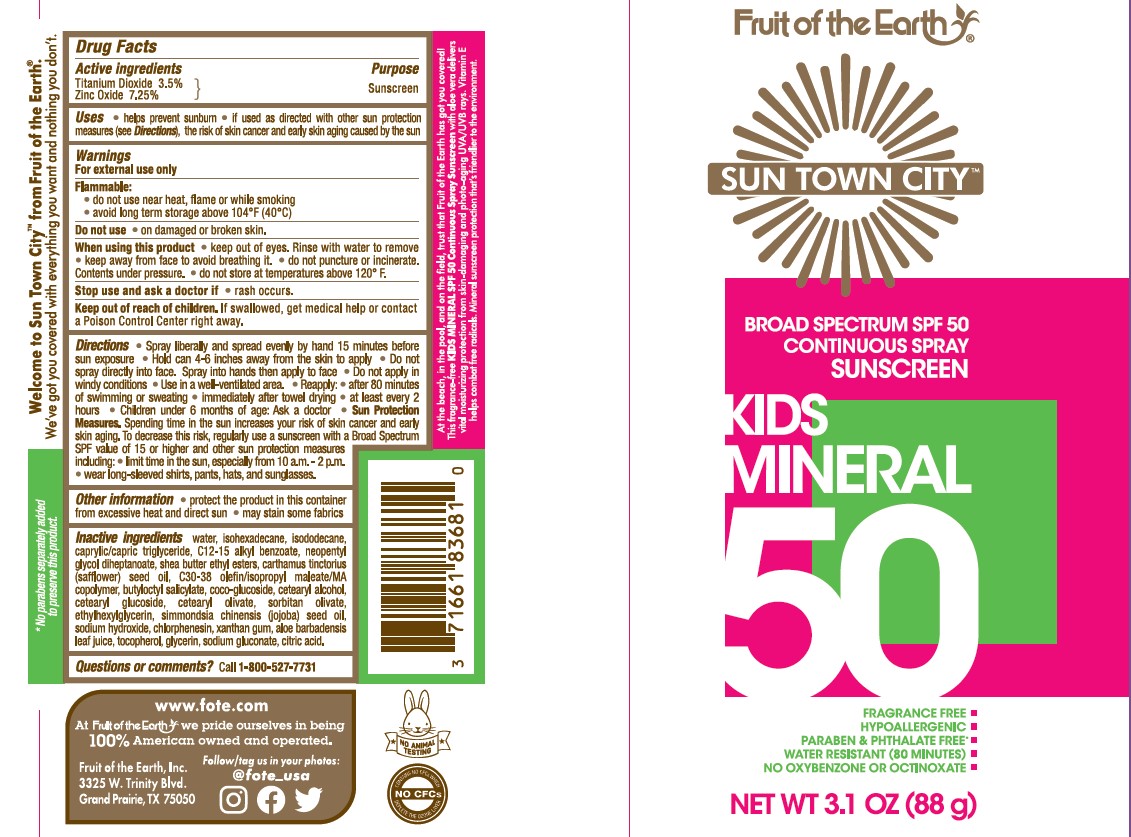 DRUG LABEL: Fruit of the Earth Sun Town City Baby and Kids Mineral SPF 50 Sunscreen
NDC: 62217-242 | Form: SPRAY
Manufacturer: Fruit Of The Earth, Inc.
Category: otc | Type: HUMAN OTC DRUG LABEL
Date: 20241018

ACTIVE INGREDIENTS: TITANIUM DIOXIDE 35 mg/1 g; ZINC OXIDE 72.5 mg/1 g
INACTIVE INGREDIENTS: CHLORPHENESIN; WATER; ISOHEXADECANE; SODIUM HYDROXIDE; CETYL ALCOHOL; ANHYDROUS CITRIC ACID; ALKYL (C12-15) BENZOATE; CETEARYL GLUCOSIDE; CETEARYL OLIVATE; SODIUM GLUCONATE; MEDIUM-CHAIN TRIGLYCERIDES; ISODODECANE; SORBITAN OLIVATE; COCO GLUCOSIDE; .ALPHA.-TOCOPHEROL, DL-; SAFFLOWER OIL; ALOE VERA LEAF; GLYCERIN; XANTHAN GUM; BUTYLOCTYL SALICYLATE; NEOPENTYL GLYCOL DIHEPTANOATE; JOJOBA OIL; SHEA BUTTER ETHYL ESTERS; ETHYLHEXYLGLYCERIN

Fruit of the Earth Sun Town City Baby and Kids Mineral SPF 50 Sunscreen Spray

Active ingredients

Titanium Dioxide 3.5%

Zinc Oxide 7.25%

Purpose

Sunscreen

Uses

- helps prevent sunburn
- if used as directed with other sun protection measures (see Directions), decreases the risk of skin cancer and early skin aging caused by the sun

Warnings

For external use only

FLAMMABLE:

• do not use near heat, flame or while smoking
• avoid long term storage above 104°F (40°C)

Do not use

- on damaged or broken skin

When using this product

• keep out of eyes. Rinse with water to remove.

• keep away from to avoid breathing it.

• do not puncture or incinerate. Contents under pressure.

• do not store at temperatures above 120° F.

Stop use and ask doctor if

- rash occurs.

Keep out of reach of children.

If product is swallowed, get medical help or contact a Poison Control Center right away.

Directions

• spray liberally and spread evenly by hand 15 minutes before sun exposure
• hold can 4-6 inches away from skin top apply
• do not spray into face. Spray into hand and apply to face.
• use in a well ventilated areas
reapply:
• after 80 minutes of swimming or sweating
• immediately after towel drying
• at least every 2 hours

• children under 6 months: Ask a doctor
• Sun Protection Measures. Spending time in the sun increases your risk of skin cancer and early skin aging. To decrease this risk, regularly use a sunscreen with a Broad Spectrum SPF Value of 15 or higher and other sun protection measures including:
• limit time in the sun, especially from 10 a.m. - 2 p.m.
• wear long-sleeved shirts, pants, hats, and sunglasses

Other Information

• protect the product in the container from excessive heat and direct sun
• may stain or damage some fabrics

Inactive ingredients

Water, Isohexadecane, Isododecane, Caprylic/Capric Triglyceride, C12-15 Alkyl Benzoate, Neopentyl Glycol Diheptanoate, Shea Butter Ethyl Esters, Carthamus Tinctorius (Safflower) Seed Oil, C30-38 Olefin/Isopropyl Maleate/MA Copolymer, Butyloctyl Salicylate, Coco-Glucoside, Cetearyl Alcohol, Cetearyl Glucoside, Cetearyl Olivate, Sorbitan Olivate, Ethylhexylglycerin, Simmondsia Chinensis (Jojoba) Seed Oil, Sodium Hydroxide, Chlorphenesin, Xanthan Gum, Aloe Barbadensis Leaf Juice, Tocopherol, Glycerin, Sodium Gluconate, Citric Acid.